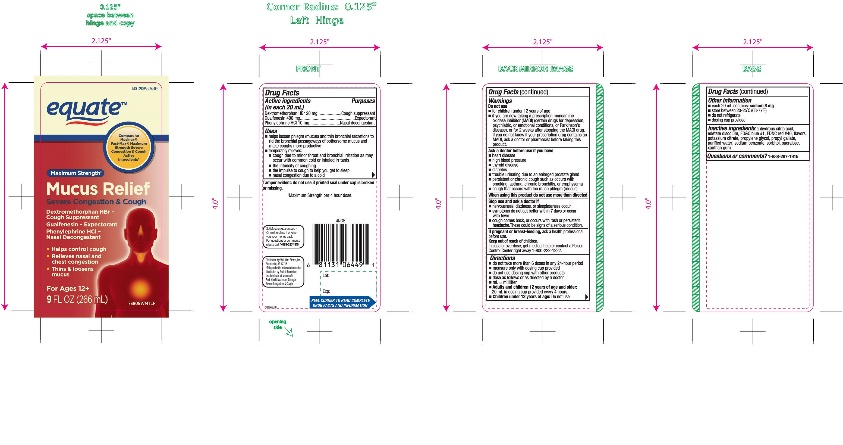 DRUG LABEL: Maximum Strength Mucus Relief Severe Congestion and Cough
NDC: 49035-774 | Form: LIQUID
Manufacturer: Wal-Mart Stores,Inc.,
Category: otc | Type: HUMAN OTC DRUG LABEL
Date: 20251202

ACTIVE INGREDIENTS: DEXTROMETHORPHAN HYDROBROMIDE 20 mg/20 mL; GUAIFENESIN 400 mg/20 mL; PHENYLEPHRINE HYDROCHLORIDE 10 mg/20 mL
INACTIVE INGREDIENTS: ANHYDROUS CITRIC ACID; EDETATE DISODIUM; FD&C BLUE NO. 1; FD&C RED NO. 40; POTASSIUM CITRATE; PROPYLENE GLYCOL; PROPYL GALLATE; WATER; SODIUM BENZOATE; SORBITOL; SUCRALOSE; XANTHAN GUM

equate™ Maximum Strength Mucus Relief Severe Congestion and Cough 9 FL OZ

Drug Facts

ACTIVE INGREDIENT

PURPOSE

Active ingredients (in each 20 mL) | Purposes
Dextromethorphan HBr 20 mg | Cough suppressant
Guaifenesin 400 mg | Expectorant
Phenylephrine HCl 10 mg | Nasal decongestant

Uses

- helps loosen phlegm (mucus) and thin bronchial secretions to rid the bronchial passageways of bothersome mucus and make coughs more productive
- temporarily relieves:
  - cough due to minor throat and bronchial irritation as may occur with the common cold or inhaled irritants
  - the intensity of coughing
  - the impulse to cough to help you get to sleep
  - nasal congestion due to a cold

Warnings

Do not use

- if you are now taking a prescription monoamine oxidase inhibitor (MAOI) (certain drugs for depression, psychiatric, or emotional conditions, or Parkinson's disease), or for 2 weeks after stopping the MAOI drug. If you do not know if your prescription drug contains an MAOI, ask a doctor or pharmacist before taking this product.

Ask a doctor before use if you have

- heart disease
- high blood pressure
- thyroid disease
- diabetes
- trouble urinating due to an enlarged prostate gland
- persistent or chronic cough such as occurs with smoking, asthma, chronic bronchitis or emphysema
- cough that occurs with too much phlegm (mucus)

When using this product

- do not use more than directed

Stop use and ask a doctor if

- nervousness, dizziness or sleeplessness occur
- symptoms do not get better within 7 days or occur with fever
- cough lasts more than 7 days, comes back, or occurs with fever, rash or headache that lasts. These could be signs of a serious condition.

PREGNANCY OR BREAST FEEDING

If pregnant or breast-feeding,ask a health professional before use.

Keep out of reach of children.In case of overdose, get medical help or contact a Poison Control Center right away. (1-800-222-1222)

Directions

- do not take more than 6 doses in any 24-hour period
- measure only with dosing cup provided
- do not use dosing cup with other products
- dose as follows or as directed by a doctor
- mL = milliliter
- Adults and children 12 years of age and older:20 mL in dosing cup provided every 4 hours.
- Children under 12 years of age:Do not use.

Other information

- each 20 mL contains: sodium 8 mg
- low sodium
- store at room temperature
- do not refrigerate
- dosing cup provided

Inactive ingredients

anhydrous citric acid, edetate disodium, FD&C Blue #1, FD&C red #40, flavors, potassium citrate, propylene glycol, propyl gallate, purified water, sodium benzoate, sorbitol, sucralose, xanthan gum

Questions or comments?

1-888-287-1915

PRINCIPAL DISPLAY PANEL

NDC 49035-774-09

Compare to Mucinex® Fast- Max® Maximum Strength Severe Congestion & Cough Active Ingredients*

Maximum Strength‡

Mucus Relief

Severe Congestion & Cough

Dextromethorphan HBr - Cough Suppressant
Guaifenesin - Expectorant
Phenylephrine HCl - Nasal Decongestant

- Helps control cough
- Relieves nasal and chest congestion
- Thins & loosens mucus

For Ages 12+

9 FL OZ (266 mL)

Tamper evident: do not use if printed seal under cap is broken or missing.

‡Maximum Strength per 4 hour dose.

Satisfaction guaranteed- Or we’ll replace it or give you your money back.

For questions or comments, please call

1-888-287-1915.

Distributed by: Wal-Mart Stores, Inc.,

Bentonville, AR 72716

*This product is not manufactured or distributed by Reckitt Benckiser, the distributor of Mucinex® Fast -Max® Maximum Strength Severe Congestion & Cough.